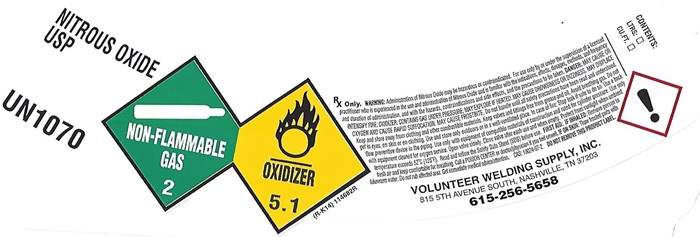 DRUG LABEL: NITROUS OXIDE
NDC: 53511-003 | Form: GAS
Manufacturer: Volunteer Welding Supply Inc
Category: prescription | Type: HUMAN PRESCRIPTION DRUG LABEL
Date: 20251126

ACTIVE INGREDIENTS: NITROUS OXIDE 99 L/100 L

Nitrous Oxide

NITROUS OXIDE USP LABEL

NITROUS OXIDE USP UN1070

NON-FLAMMABLE GAS 2 OXIDIZER 5.1

(R-K14) 114682R

Rx only. WARNING: Administration of Nitrous Oxide may be hazardous or contraindicated. For use only by or under supervision of a licensed practitioner who is experienced in the use and administration of Nitrous Oxide and is familiar with the indications, effects, dosages, methods, and frequency and duration of administration, and with the hazards, contraindications, and side effects and the precautions to be taken . DANGER: HIGH PRESSURE OXIDIZING LIQUID AND GAS. VIGOROUSLY ACCELERATES COMBUSTION. CAN CAUSE RAPID SUFFOCATION. CAN CAUSE ANESTHETIC EFFECTS. MAY CAUSE FROSTBITE. Avoid breathing gas. Store and use with adequate ventilation. Keep oil and grease away. Use only equipment cleaned for oxygen and rated for cylinder pressure. Do not get liquid in eyes, on skin, and clothing. Cylinder temperatures should not exceed 52C (125F). Open valve slowly. Close valve after each use and when empty. Use back flow preventive device in the piping. Use in accordance with the Material Safety Data Sheet (MSDS). FIRST AID: IF INHALED: Remove person to fresh air and keep comfortable for breathing. Call a POISON CENTER or doctor/physician if you feel unwell. IF ON SKIN: Thaw frosted parts with lukewarm water. Do not rub affected area. Get immediate medical advice/attention. WARNING: This product contains a chemical known to the state of California to cause birth defects or other reproductive harm. CAS: 10024-97-2

DO NOT REMOVE THIS PRODUCT LABEL.

VOLUNTEER WELDING SUPPLY, INC.

815 5TH AVENUE SOUTH, NASHVILLE, TN 37203

615-256-5658

CONTENTS: _______________________________ LITERS ___ CU FT ____